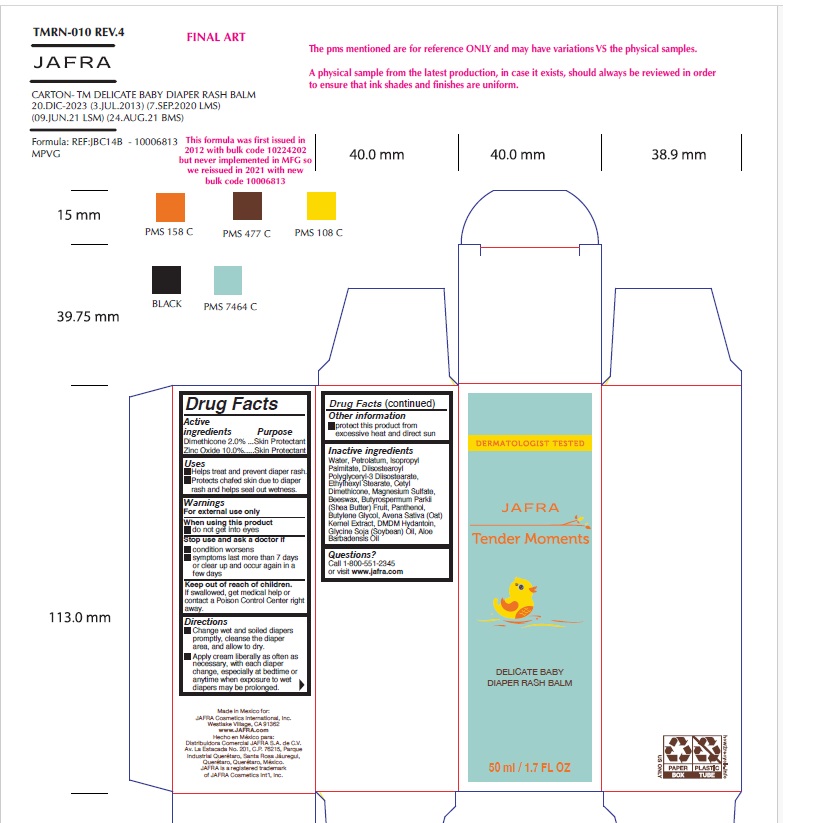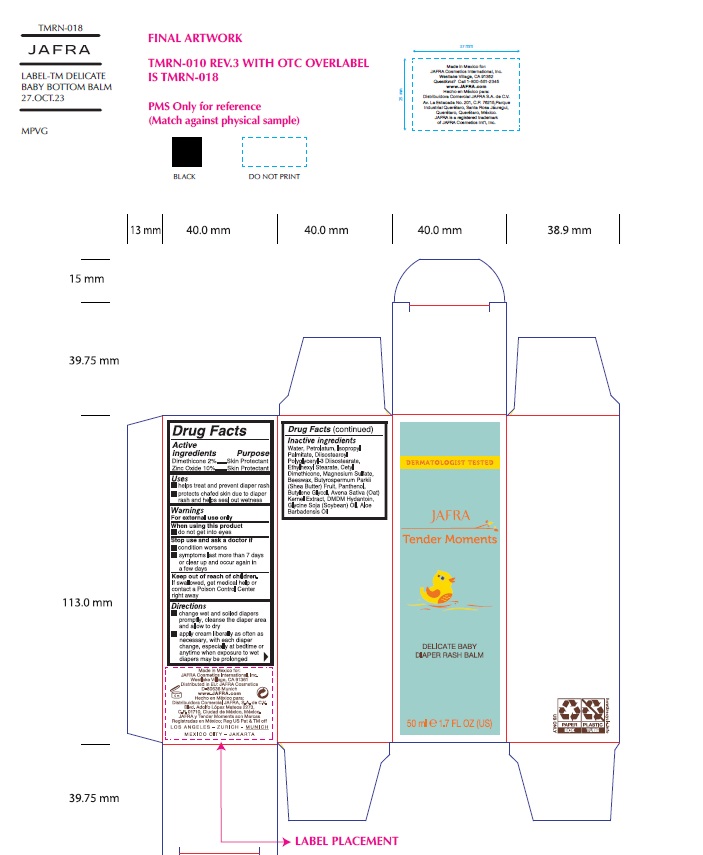 DRUG LABEL: Tender Moments Delicate Baby Diaper Rash Balm
NDC: 68828-700 | Form: CREAM
Manufacturer: Distribuidora Comercial Jafra, S.A. de C.V.
Category: otc | Type: HUMAN OTC DRUG LABEL
Date: 20250102

ACTIVE INGREDIENTS: DIMETHICONE 2 g/100 mL; ZINC OXIDE 10 g/100 mL
INACTIVE INGREDIENTS: WATER; PETROLATUM; ISOPROPYL PALMITATE; DIISOSTEAROYL POLYGLYCERYL-3 DIMER DILINOLEATE; ETHYLHEXYL STEARATE; CETYL DIMETHICONE 25; MAGNESIUM SULFATE, UNSPECIFIED FORM; WHITE WAX; SHEA BUTTER; PANTHENOL; BUTYLENE GLYCOL; OAT; DMDM HYDANTOIN; SOYBEAN OIL; ALOE

Tender Moments Delicate Baby Diaper Rash Balm

Active Ingredients

Dimethicone 2.0%, Zinc Oxide 10.0%

Purpose

Skin Protectant

Uses

▪ Helps treat and prevent diaper rash
▪ Protects chafed skin due to diaper rash and helps seal out wetness

Warnings

For external use only
When using this product do not get into eyes.
Stop use and ask a doctor if
▪ condition worsens
▪ symptoms last more than 7 days or clear up and occur again in a few days
Keep out of reach of children. If swallowed, get medical help or contact a Poison Control Center right away.

Directions

▪ Change wet and soiled diapers promptly, cleanse the diaper area and allow to dry
▪ Apply cream liberally as often as necessary, with each diaper change, especially at bedtime or anytime when exposure to wet diapers may be prolonged

Other information

- protect this product from excessive heat and direct sun

Inactive Ingredients

Water, Petrolatum, Isopropyl Palmitate, Diisostearoyl Polyglyceryl-3 Diisostearate, Ethylhexyl Stearate, Cetyl Dimethicone, Magnesium Sulfate, Beeswax, Butyrospermum Parkii (Shea Butter) Fruit, Panthenol, Butylene Glycol, Avena Sativa (Oat) Kernel Extract, DMDM Hydantoin, Glycine Soja (Soybean) Oil, Aloe Barbadensis Oil

Questions?Call 1-800-551-2345 or visit www.jafra .com